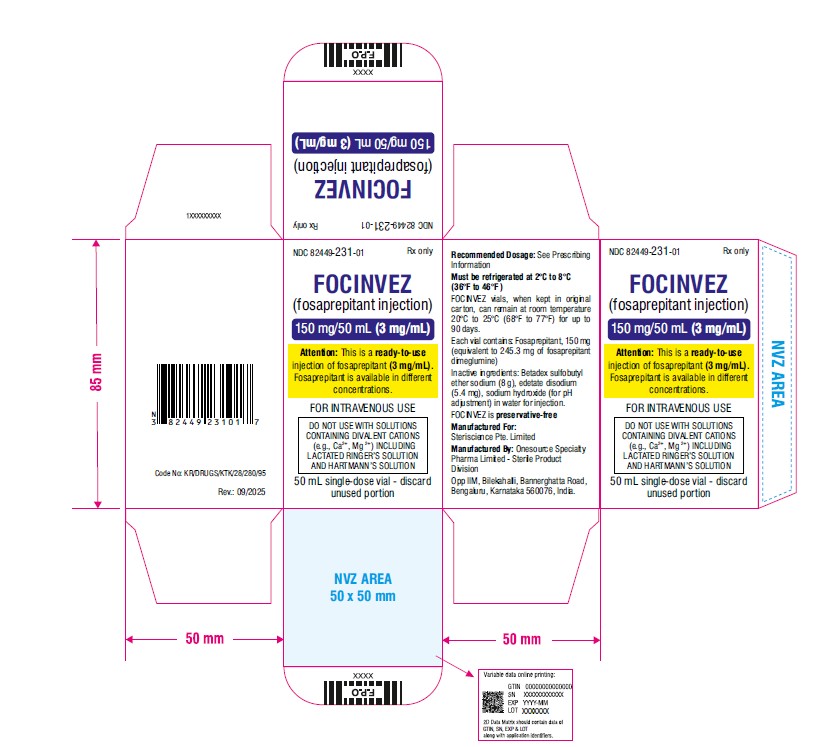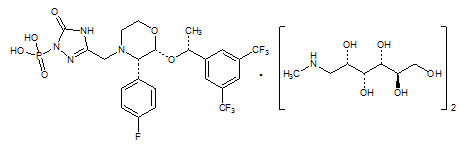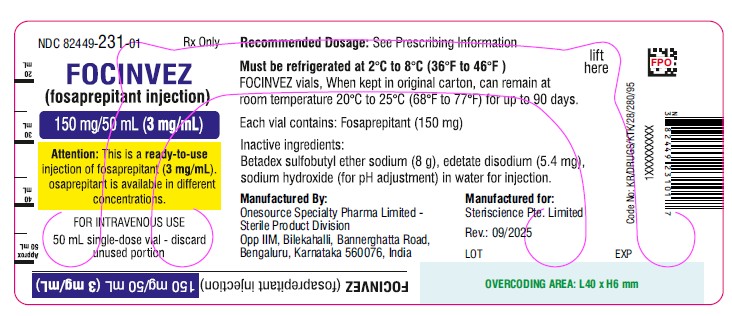 DRUG LABEL: FOCINVEZ
NDC: 82449-231 | Form: INJECTION
Manufacturer: Steriscience Specialties Private Limited
Category: prescription | Type: HUMAN PRESCRIPTION DRUG LABEL
Date: 20251010

ACTIVE INGREDIENTS: FOSAPREPITANT DIMEGLUMINE 150 mg/50 mL
INACTIVE INGREDIENTS: EDETATE DISODIUM 5.4 mg/50 mL; BETADEX SULFOBUTYL ETHER SODIUM 8 g/50 mL; SODIUM HYDROXIDE; WATER

HIGHLIGHTS OF PRESCRIBING INFORMATION

These highlights do not include all the information needed to use FOCINVEZ safely and effectively. See full prescribing information for FOCINVEZ.
FOCINVEZ (fosaprepitant injection) for intravenous use
Initial U.S. Approval: 2008

1 INDICATIONS AND USAGE

FOCINVEZ is a substance P/neurokinin-1 (NK1) receptor antagonist, indicated in adults and pediatric patients 6 months of age and older, in combination with other antiemetic agents, for the prevention of (1):

- acute and delayed nausea and vomiting associated with initial and repeat courses of highly emetogenic cancer chemotherapy (HEC) including high-dose cisplatin.
- delayed nausea and vomiting associated with initial and repeat courses of moderately emetogenic cancer chemotherapy (MEC).

Limitations of Use (1)

- FOCINVEZ has not been studied for treatment of established nausea and vomiting.

2 DOSAGE AND ADMINISTRATION

Recommended Adult Dosage (2.1)

- FOCINVEZ 150mg on Day 1 as an intravenous infusion over 20 to 30 minutes;
- Complete the infusion approximately 30 minutes prior to chemotherapy.

Recommended Dosage for Pediatric Patients (6 months to 17 years) Weighing at Least 6 kg (2.2)

- See Full Prescribing Information for pediatric dosage regimens by age.
- single dose chemotherapy regimens:single dose of FOCINVEZ on Day 1.
- single or multi-day chemotherapy regimens:3-day regimen of FOCINVEZ on Day 1 and aprepitant capsules or aprepitant for oral suspension on Days 2 and 3.
- Administer FOCINVEZ through a central venous catheter on Day 1 as an intravenous infusion over 30 minutes (12 years to 17 years) or 60 minutes (6 months to less than 12 years).
- Complete the infusion approximately 30 minutes prior to chemotherapy.

Concomitant Antiemetics

- See Full Prescribing Information for additional information. (2.1, 2.2)

3 DOSAGE FORMS AND STRENGTHS

Injection: 150 mg/50 mL (3 mg/mL) of fosaprepitant, in a single-dose vial. (3)

4 CONTRAINDICATIONS

- Known hypersensitivity to any component of this drug. (4, 5.2)
- Concurrent use with pimozide. (4)

5 WARNINGS AND PRECAUTIONS

- CYP3A4 Interactions: Fosaprepitant is a weak inhibitor of CYP3A4, and aprepitant, the active moiety, is a substrate, inhibitor, and inducer of CYP3A4; see Full Prescribing Information for recommendations regarding contraindications, risk of adverse reactions, and dosage adjustment of FOCINVEZ and concomitant drugs. (4, 5.1, 7.1, 7.2)
- Hypersensitivity Reactions (including anaphylaxis and anaphylactic shock): May occur during or soon after infusion. If symptoms occur, discontinue the drug. Do not reinitiate FOCINVEZ if symptoms occur with previous use. (4, 5.2)
- Infusion Site Reactions (including thrombophlebitis, necrosis, and vasculitis): Majority of reactions reported in patients receiving vesicant chemotherapy. Avoid infusion into small veins. Discontinue infusion and administer treatment if a severe reaction develops. (5.3)
- Warfarin (a CYP2C9 substrate): Risk of decreased INR of prothrombin time; monitor INR in 2–week period, particularly at 7 to 10 days, following initiation of FOCINVEZ. (5.4, 7.1)
- Hormonal Contraceptives: Efficacy of contraceptives may be reduced during treatment and for 1 month following administration of the last dose of either fosaprepitant or oral aprepitant. Use effective alternative or back-up methods of contraception. (5.5, 7.1, 8.3)

6 ADVERSE REACTIONS

- Most common adverse reactions in adults (≥2%) are: fatigue, diarrhea, neutropenia, asthenia, anemia, peripheral neuropathy, leukopenia, dyspepsia, urinary tract infection, pain in extremity. (6.1)
- Adverse reactions in pediatric patients are similar to adults.

To report SUSPECTED ADVERSE REACTIONS, contact Steriscience at (1-888-278-1784) or FDA at 1-800-FDA-1088 or www.fda.gov/medwatch.

7 DRUG INTERACTIONS

See Full Prescribing Information for a list of clinically significant drug interactions. (4, 5.1, 5.4, 5.5, 7.1, 7.2)

Additional pediatric use information is approved for Merck Sharp & Dohme LLC’s EMEND (fosaprepitant) for injection. However, due to Merck Sharp & Dohme LLC’s marketing exclusivity rights, this drug product is not labeled with that information.

FULL PRESCRIBING INFORMATION

1 INDICATIONS AND USAGE

FOCINVEZ, in combination with other antiemetic agents, is indicated in adults and pediatric patients 6 months of age and older for the prevention of:

- acute and delayed nausea and vomiting associated with initial and repeat courses of highly emetogenic cancer chemotherapy (HEC) including high-dose cisplatin.
- delayed nausea and vomiting associated with initial and repeat courses of moderately emetogenic cancer chemotherapy (MEC).

Limitations of Use

- FOCINVEZ has not been studied for the treatment of established nausea and vomiting.

2 DOSAGE AND ADMINISTRATION

2.1 Recommended Dosage for the Prevention of Nausea and Vomiting Associated with HEC and MEC in Adult Patients

The recommended dosage of FOCINVEZ, dexamethasone, and a 5-HT3 antagonist for the prevention of nausea and vomiting associated with administration of HEC or MEC in adults is shown in Table 1 or Table 2, respectively. Administer FOCINVEZ as an intravenous infusion on Day 1 over 20 to 30 minutes, completing the infusion approximately 30 minutes prior to chemotherapy.

Table 1 Recommended Adult Dosage for the Prevention of Nausea and Vomiting Associated with HEC
 | Day 1 | Day 2 | Day 3 | Day 4
FOCINVEZa | 150 mg intravenously over 20 to 30 minutes | none | none | none
Dexamethasoneb | 12 mg orally | 8 mg orally | 8 mg orally twice daily | 8 mg orally twice daily
5-HT3 antagonist | See selected 5-HT3antagonist prescribing information for the recommended dosage | none | none | none

aThe concentration of FOCINVEZ is 3 mg/mL
bAdminister dexamethasone 30 minutes prior to chemotherapy treatment on Day 1 and in the morning on Days 2 through 4. Also administer dexamethasone in the evenings on Days 3 and 4. A 50% dosage reduction of dexamethasone on Days 1 and 2 is recommended to account for a drug interaction with FOCINVEZ [see Clinical Pharmacology (12.3)] .

Table 2 Recommended Adult Dosage for the Prevention of Nausea and Vomiting Associated with MEC
 | Day 1
FOCINVEZa | 150 mg intravenously over 20 to 30 minutes
Dexamethasoneb | 12 mg orally
5-HT3 antagonist | See selected 5-HT3antagonist prescribing information for the recommended dosage

a The concentration of FOCINVEZ is 3 mg/mL.
b Administer dexamethasone 30 minutes prior to chemotherapy treatment on Day 1. A 50% dosage reduction of dexamethasone is recommended to account for a drug interaction with FOCINVEZ [see Clinical Pharmacology (12.3)] .

2.2 Recommended Dosage for the Prevention of Nausea and Vomiting Associated with HEC and MEC in Pediatric Patients

The recommended pediatric dosage regimens of FOCINVEZ, to be administered with a 5-HT3 antagonist, with or without a corticosteroid, for the prevention of nausea and vomiting associated with administration of single or multi-day chemotherapy regimens of HEC or MEC, are shown in Tables 3 and 4. Single-day chemotherapy regimens include those regimens in which HEC or MEC is administered for a single day only. Multi-day chemotherapy regimens include chemotherapy regimens in which HEC or MEC is administered for 2 or more days.

FOCINVEZ Dosage Regimens for Use with Single-Day Chemotherapy Regimens

For pediatric patients weighing at least 6 kg receiving single-day HEC or MEC, FOCINVEZ may be administered as:

- a single dose regimen of FOCINVEZ infused through a central venous catheter on Day 1, as shown in Table 3; or
- as a 3-day fosaprepitant/aprepitant regimen consisting of FOCINVEZ as an intravenous infusion through a central venous catheter on Day 1 and aprepitant capsules or aprepitant for oral suspension on Days 2 and 3, as shown in Table 4.

Administer FOCINVEZ on Day 1 over 30 minutes (12 years to 17 years) or 60 minutes (6 months to less than 12 years), completing the infusion approximately 30 minutes prior to chemotherapy.

Table 3 FOCINVEZ Single Dose Regimen for the Prevention of Nausea and Vomiting Associated with Single-Day Regimens of HEC or MEC in Pediatric Patients 6 Monthsa to 17 Years
Drug | Age | Regimen
FOCINVEZb | 12 Years to 17 Years | 150 mg intravenously over 30 minutes
FOCINVEZb | 2 Years to less than 12 Years | 4 mg/kg (maximum dose 150 mg) intravenously over 60 minutes
FOCINVEZb | 6 Months to less than 2 Years | 5 mg/kg (maximum dose 150 mg) intravenously over 60 minutes
Dexamethasonec | 6 Months to 17 Years | If a corticosteroid, such as dexamethasone, is co-administered, administer 50% of the recommended corticosteroid dose on Days 1 and 2.
5-HT3 antagonist | 6 Months to 17 Years | See selected 5-HT3antagonist prescribing information for the recommended dosage

aDosing in pediatric patients less than 6 kg is not recommended
bThe concentration of FOCINVEZ is 3mg/mL.
cAdminister dexamethasone 30 minutes prior to chemotherapy treatment on Day 1

FOCINVEZ Dosage Regimen for Use with Multi-Day Chemotherapy Regimens

For pediatric patients weighing at least 6 kg receiving multi-day regimens of HEC or MEC, administer FOCINVEZ as an intravenous infusion through a central venous catheter on Day 1 and aprepitant capsules or aprepitant for oral suspension on Days 2 and 3, as shown in Table 4.

Administer FOCINVEZ over 30 minutes (12 years to 17 years) or 60 minutes (6 months to less than 12 years), completing the infusion approximately 30 minutes prior to chemotherapy.

Table 4. 3-Day Fosaprepitant/Aprepitant Dosage Regimen for Prevention of Nausea and Vomiting Associated with Single or Multi-day Regimens of HEC or MEC in Pediatric Patients 6 Monthsa to 17 Years
Age Group | Drug | Day 1 | Day 2 | Day 3
12 Years to 17 Years | FOCINVEZb | 115 mg intravenously over 30 minutes | - | -
 | Aprepitant capsulesc | - | 80 mg orally | 80 mg orally
6 Months to Less than 12 Years | FOCINVEZ | 3 mg/kg (maximum dose 115 mg) intravenously over 60 minutes | - | -
 | Aprepitant for oral suspensiond | - | 2 mg/kg orally (maximum 80 mg) | 2 mg/kg orally (maximum 80 mg)
6 Months to 17 Years | Dexamethasonee | If a corticosteroid, such as dexamethasone, is co-administered, administer 50% of the recommended corticosteroid dose on Days 1 through 4
6 Months to 17 Years | 5-HT3 antagonist | See selected 5-HT3 antagonist prescribing information for the recommended dosage

aDosing in pediatric patients less than 6 kg is not recommended
bThe concentration of FOCINVEZ is 3 mg/mL.
cFor patients 12 years to 17 years who cannot swallow oral capsules, aprepitant for oral suspension can be used instead.
dFor patients less than 12 years of age who weigh at least 40 kg and who are able to swallow oral capsules, aprepitant capsules can be used on Days 2 and 3.
eAdminister dexamethasone 30 minutes prior to chemotherapy treatment on Day 1.

Additional pediatric use information is approved for Merck Sharp & Dohme LLC’s EMEND (fosaprepitant) for injection. However, due to Merck Sharp & Dohme LLC’s marketing exclusivity rights, this drug product is not labeled with that information.

2.3 Preparation of FOCINVEZ

FOCINVEZ is ready-to-use for intravenous infusion. The concentration of FOCINVEZ is 3 mg/mL.

Determine the volume to be administered from the injection vial directly based on the recommended dose [see Dosage and Administration (2.1, 2.2)].

Adults
The entire volume of the vial (50 mL) should be administered.

Pediatrics
In patients 12 years and older, the volume to be administered is calculated as follows:

- Volume to administer (mL) = the recommended dose (mg) / 3 (mg/mL)*

In patients 6 months to less than 12 years, the volume to be administered is calculated as follows:

- Volume to administer (mL) = the recommended dose (mg/kg) x weight (kg) / 3 (mg/mL)*
- Note: Do not exceed the maximum dose [see Dosage and Administration (2.2)]
- In pediatric patients, the entire volume in vial may NOT be required. Discard the unused portion.
- * The recommended dose of FOCINVEZ is based on the patient’s age and weight. The concentration of FOCINVEZ is 3 mg/mL.
- Parenteral drug products should be inspected visually for particulate matter and discoloration prior to administration whenever solution and container permit. Do not use if solution is cloudy, contains precipitates, or if the red flip top cap is not intact.
- Allow FOCINVEZ to come to room temperature before use if the injection is NOT stored at room temperature.
- Use a vented infusion set when FOCINVEZ is infused from the bottle.
- The vial hanger can be separated from the vial label.
- Gently invert the bottle and hang the bottle using the attached hanger and start infusion.
- Caution: Do not mix FOCINVEZ with solutions for which physical and chemical compatibility have not been established. FOCINVEZ is incompatible with any solutions containing divalent cations (e.g., Ca^2+, Mg^2+), including Lactated Ringer’s Solution and Hartmann's Solution.

FOCINVEZ is compatible with 0.9% Sodium Chloride Injection. Always flush the IV set with 0.9% sodium chloride to remove any residual medication. Utilization of IV set without flushing may cause precipitation.

3 DOSAGE FORMS AND STRENGTHS

Injection: 150 mg/50 mL (3 mg/mL) of fosaprepitant, a clear and colorless solution, in a single-dose vial.

4 CONTRAINDICATIONS

FOCINVEZ is contraindicated in patients:

- who are hypersensitive to any component of the product. Hypersensitivity reactions including anaphylactic reactions, flushing, erythema, and dyspnea have been reported [see Warnings and Precautions (5.2), and Adverse Reactions (6.2)] .
- taking pimozide. Inhibition of CYP3A4 by aprepitant, the active moiety, could result in elevated plasma concentrations of this drug, which is a CYP3A4 substrate, potentially causing serious or life-threatening reactions, such as QT prolongation, a known adverse reaction of pimozide [see Warnings and Precautions (5.1)] .

5 WARNINGS AND PRECAUTIONS

5.1 Clinically Significant CYP3A4 Drug Interactions

Fosaprepitant, a prodrug of aprepitant, is a weak inhibitor of CYP3A4, and aprepitant is a substrate, inhibitor, and inducer of CYP3A4.

- Use of FOCINVEZ with other drugs that are CYP3A4 substrates, may result in increased plasma concentration of the concomitant drug.
- Use of pimozide with FOCINVEZ is contraindicated due to the risk of significantly increased plasma concentrations of pimozide, potentially resulting in prolongation of the QT interval, a known adverse reaction of pimozide [see Contraindications (4)] .
- Use of FOCINVEZ with strong or moderate CYP3A4 inhibitors (e.g., ketoconazole, diltiazem) may increase plasma concentrations of aprepitant and result in an increased risk of adverse reactions related to FOCINVEZ.
- Use of FOCINVEZ with strong CYP3A4 inducers (e.g., rifampin) may result in a reduction in aprepitant plasma concentrations and decreased efficacy of FOCINVEZ.

See Table 7 and Table 8 for a listing of potentially significant drug interactions [see Drug Interactions (7.1, 7.2)] .

5.2 Hypersensitivity Reactions

Serious hypersensitivity reactions, including anaphylaxis and anaphylactic shock, during or soon after infusion of fosaprepitant have occurred. Symptoms including flushing, erythema, dyspnea, hypotension and syncope have been reported [see Adverse Reactions (6.2)] .

Monitor patients during and after infusion. If hypersensitivity reactions occur, discontinue the infusion and administer appropriate medical therapy. Do not reinitiate FOCINVEZ in patients who experience these symptoms with previous use [see Contraindications (4)] .

5.3 Infusion Site Reactions

Infusion site reactions (ISRs) have been reported with the use of intravenous fosaprepitant [see Adverse Reactions (6.1)] . The majority of severe ISRs, including thrombophlebitis and vasculitis, were reported with concomitant vesicant (anthracycline-based) chemotherapy administration, particularly when associated with extravasation. Necrosis was also reported in some patients with concomitant vesicant chemotherapy. Most ISRs occurred with the first, second or third exposure to single doses of intravenous fosaprepitant and in some cases, reactions persisted for two weeks or longer. Treatment of severe ISRs consisted of medical, and in some cases surgical, intervention.

Avoid infusion of FOCINVEZ into small veins or through a butterfly catheter. If a severe ISR develops during infusion, discontinue the infusion and administer appropriate medical treatment.

5.4 Decrease in INR with Concomitant Warfarin

Coadministration of fosaprepitant with warfarin, a CYP2C9 substrate, may result in a clinically significant decrease in the International Normalized Ratio (INR) of prothrombin time [see Clinical Pharmacology (12.3)] . Monitor the INR in patients on chronic warfarin therapy in the 2-week period, particularly at 7 to 10 days, following initiation of FOCINVEZ with each chemotherapy cycle [see Drug Interactions (7.1)] .

5.5 Risk of Reduced Efficacy of Hormonal Contraceptives

Upon coadministration with fosaprepitant, the efficacy of hormonal contraceptives may be reduced during administration of and for 28 days following the last dose of fosaprepitant [see Clinical Pharmacology (12.3)] . Advise patients to use effective alternative or back-up methods of contraception during treatment with FOCINVEZ and for 1 month following administration of the last dose of fosaprepitant or oral aprepitant [see Drug Interactions (7.1), and Use in Specific Populations (8.3)] .

6 ADVERSE REACTIONS

The following clinically significant adverse reactions are described elsewhere in the labeling:

- Hypersensitivity Reactions [see Warnings and Precautions (5.2)]
- Infusion Site Reactions [see Warnings and Precautions (5.3)]

6.1 Clinical Trials Experience

Because clinical trials are conducted under widely varying conditions, adverse reaction rates observed in the clinical trials of a drug cannot be directly compared to rates in the clinical trials of another drug and may not reflect the rates observed in clinical practice.

The safety of FOCINVEZ has been established from adequate and well-controlled studies of another intravenous formulation of fosaprepitant [see Clinical Studies (14)] . Below is a display of the adverse reactions of fosaprepitant in these studies.

The overall safety of intravenous fosaprepitant was evaluated in approximately 1800 adult and pediatric patients.

Adverse Reactions in Adults for the Prevention of Nausea and Vomiting Associated with MEC
In an active-controlled clinical trial in patients receiving MEC, safety was evaluated in 504 patients receiving a single dose of intravenous fosaprepitant in combination with ondansetron and dexamethasone (intravenous fosaprepitant regimen) compared to 497 patients receiving ondansetron and dexamethasone alone (standard therapy). The most common adverse reactions are listed in Table 6.

Table 6 Most Common Adverse Reactions in Patients Receiving MECa

 | Intravenous fosaprepitant, ondansetron, and dexamethasoneb (N=504) | Ondansetron and dexamethasonec (N=497)
fatigue | 15% | 13%
diarrhea | 13% | 11%
neutropenia | 8% | 7%
asthenia | 4% | 3%
anemia | 3% | 2%
peripheral neuropathy | 3% | 2%
leukopenia | 2% | 1%
dyspepsia | 2% | 1%
urinary tract infection | 2% | 1%
pain in extremity | 2% | 1%

a Reported in ≥2% of patients treated with the intravenous fosaprepitant regimen and at a greater incidence than standard therapy (ondansetron and dexamethasone alone).
b Intravenous fosaprepitant regimen
c Standard therapy

Infusion-site reactions were reported in 2.2% of patients treated with the intravenous fosaprepitant regimen compared to 0.6% of patients treated with standard therapy. The infusion-site reactions included: infusion-site pain (1.2%, 0.4%), injection-site irritation (0.2%, 0.0%), vessel puncture-site pain (0.2%, 0.0%), and infusion-site thrombophlebitis (0.6%, 0.0%), reported in the intravenous fosaprepitant regimen compared to standard therapy, respectively.

Adverse Reactions in Adults for the Prevention of Nausea and Vomiting Associated with HEC
In an active-controlled clinical study in patients receiving HEC, safety was evaluated for 1143 patients receiving a single dose of intravenous fosaprepitant compared to 1169 patients receiving the 3-day regimen of oral aprepitant [see Clinical Studies (14.1)] . The safety profile was generally similar to that seen in the MEC study with fosaprepitant and prior HEC studies with aprepitant. However, infusion-site reactions occurred at a higher incidence in patients in the fosaprepitant group (3.0%) compared to those in the aprepitant group (0.5%). The following additional infusion-site reactions occurred in the HEC study and were not reported in the MEC study described above: infusion-site erythema (0.5%, 0.1%), infusion-site pruritus (0.3%, 0.0%), and infusion-site induration (0.2%, 0.1%), reported in the fosaprepitant group compared to the aprepitant group, respectively.

Adverse Reactions in Pediatric Patients 6 Months to 17 Years of Age for the Prevention of Nausea and Vomiting Associated with HEC or MEC
Single-Dose Intravenous Fosaprepitant Regimen
The safety of a single dose of intravenous fosaprepitant in pediatric patients (6 months to 17 years) was evaluated in two active-controlled and a single-arm clinical study in patients who received either HEC or MEC. Patients also received ondansetron with or without dexamethasone. The adverse reaction profile was similar to adults. The safety analysis included 69 pediatric patients who received the recommended dose. An additional 70 patients received a single, higher-than-recommended dose. The most common adverse reactions that occurred in >15% of patients who received the recommended dose were anemia, neutropenia, thrombocytopenia, and febrile neutropenia.

3-Day Intravenous Fosaprepitant/Oral Aprepitant/Oral Aprepitant Regimen
In pediatric patients (12 to 17 years), the safety of the 3-day intravenous fosaprepitant/oral aprepitant/oral aprepitant regimen was evaluated in a single-arm clinical study including 12 patients who received a regimen of either HEC or MEC. In pediatric patients 6 months to 12 years of age, the safety of the 3-day regimen was not directly evaluated. The safety of a single-dose of intravenous fosaprepitant (3 mg/kg) administered on day 1 of the 3-day regimen was evaluated in one active-controlled and one single-arm study including 48 patients who received a regimen of either HEC or MEC.

In these clinical studies, pediatric patients also received ondansetron with or without dexamethasone. The adverse reaction profile was similar to adults and pediatric patients receiving a single dose of intravenous fosaprepitant.

Because fosaprepitant is converted to aprepitant, those adverse reactions associated with aprepitant might also be expected to occur with intravenous fosaprepitant. See the full prescribing information for aprepitant capsules for complete safety information regarding studies performed with oral aprepitant.

Additional pediatric use information is approved for Merck Sharp & Dohme LLC’s EMEND (fosaprepitant) for injection. However, due to Merck Sharp & Dohme LLC’s marketing exclusivity rights, this drug product is not labeled with that information.

6.2 Postmarketing Experience

The following adverse reactions have been identified during post-approval use of fosaprepitant. Because these reactions are reported voluntarily from a population of uncertain size, it is not always possible to reliably estimate their frequency or establish a causal relationship to drug exposure.

Skin and subcutaneous tissue disorders: pruritus, rash, urticaria, Stevens-Johnson syndrome/toxic epidermal necrolysis [see Warnings and Precautions (5.2)] .

Immune system disorders:hypersensitivity reactions including anaphylaxis and anaphylactic shock [see Contraindications (4), Warnings and Precautions (5.2)] .

Nervous system disorders:ifosfamide-induced neurotoxicity reported after fosaprepitant and ifosfamide coadministration.

7 DRUG INTERACTIONS

7.1 Effect of Fosaprepitant/Aprepitant on the Pharmacokinetics of Other Drugs

When administered intravenously, fosaprepitant, a prodrug of aprepitant, is converted to aprepitant within 30 minutes. Therefore, drug interactions following administration of FOCINVEZ are likely to occur with drugs that interact with oral aprepitant.

Fosaprepitant, given as a single 150-mg dose, is a weak inhibitor of CYP3A4, and the weak inhibition of CYP3A4 continues for 2 days after single dose administration. Single dose fosaprepitant does not induce CYP3A4. Aprepitant is a substrate, an inhibitor, and an inducer of CYP3A4. Aprepitant is also an inducer of CYP2C9 [see Clinical Pharmacology (12.3)] .

Some substrates of CYP3A4 are contraindicated with FOCINVEZ [see Contraindications (4)] . Dosage adjustment of some CYP3A4 and CYP2C9 substrates may be warranted, as shown in Table 7.

Table 7 Effects of Fosaprepitant/Aprepitant on the Pharmacokinetics of Other Drugs

CYP3A4 Substrates
Pimozide
Clinical Impact | Increased pimozide exposure
Intervention | FOCINVEZ is contraindicated [see Contraindications (4)] .
Benzodiazepines
Clinical Impact | Increased exposure to midazolam or other benzodiazepines metabolized via CYP3A4 (alprazolam, triazolam) may increase the risk of adverse reactions [see Clinical Pharmacology (12.3)] .
Intervention | Monitor for benzodiazepine-related adverse reactions.
Dexamethasone
Clinical Impact | Increased dexamethasone exposure [see Clinical Pharmacology (12.3)] .
Intervention | Reduce the dose of oral dexamethasone by approximately 50% [see Dosage and Administration (2.1)].
Methylprednisolone
Clinical Impact | Increased methylprednisolone exposure [see Clinical Pharmacology (12.3)].
Intervention | Reduce the dose of oral methylprednisolone by approximately 50% on Days 1 and 2 for patients receiving HEC and on Day 1 for patients receiving MEC. Reduce the dose of intravenous methylprednisolone by 25% on Days 1 and 2 for patients receiving HEC and on Day 1 for patients receiving MEC.
Chemotherapeutic agents that are metabolized by CYP3A4
Clinical Impact | Increased exposure of the chemotherapeutic agent may increase the risk of adverse reactions [see Clinical Pharmacology (12.3)].
Intervention | Vinblastine, vincristine, or ifosfamide or other chemotherapeutic agents; - Monitor for chemotherapeutic-related adverse reactions.; Etoposide, vinorelbine, paclitaxel, and docetaxel; - No dosage adjustment needed.
Hormonal Contraceptives
Clinical Impact | Decreased hormonal exposure during administration of and for 28 days after administration of the last dose of fosaprepitant [see Warnings and Precautions (5.5), Use in Specific Populations (8.3), and Clinical Pharmacology (12.3)] .
Intervention | Effective alternative or back-up methods of contraception (such as condoms and spermicides) should be used during treatment with FOCINVEZ and for 1 month following administration of the last dose of fosaprepitant or oral aprepitant.
Examples | birth control pills, transdermal systems, implants, and certain intrauterine systems
CYP2C9 Substrates
Warfarin
Clinical Impact | Decreased warfarin exposure and decreased prothrombin time (INR) [see Warnings and Precautions (5.4) and Clinical Pharmacology (12.3)] .
Intervention | In patients on chronic warfarin therapy, monitor the prothrombin time (INR) in the 2-week period, particularly at 7 to 10 days, following administration of FOCINVEZ with each chemotherapy cycle.
Other
5-HT3 Antagonists
Clinical Impact | No change in the exposure of the 5-HT3antagonist [see Clinical Pharmacology (12.3)].
Intervention | No dosage adjustment needed
Examples | ondansetron, granisetron, dolasetron

7.2 Effect of Other Drugs on the Pharmacokinetics of Fosaprepitant/Aprepitant

Aprepitant is a CYP3A4 substrate [see Clinical Pharmacology (12.3)] . Co-administration of FOCINVEZ with drugs that are inhibitors or inducers of CYP3A4 may result in increased or decreased plasma concentrations of aprepitant, respectively, as shown in Table 8.

Table 8 Effects of Other Drugs on Pharmacokinetics of Fosaprepitant / Aprepitant

Moderate to Strong CYP3A4 Inhibitors
Clinical Impact | Significantly increased exposure of aprepitant may increase the risk of adverse reactions associated with FOCINVEZ [see Adverse Reactions (6.1) and Clinical Pharmacology (12.3)] .
Intervention | Avoid concomitant use of FOCINVEZ
Examples | Moderate inhibitor: diltiazem; Strong inhibitors: ketoconazole, itraconazole, nefazodone, troleandomycin, clarithromycin, ritonavir, nelfinavir
Strong CYP3A4 Inducers
Clinical Impact | Substantially decreased exposure of aprepitant in patients chronically taking a strong CYP3A4 inducer may decrease the efficacy of FOCINVEZ [see Clinical Pharmacology (12.3)].
Intervention | Avoid concomitant use of FOCINVEZ
Examples | rifampin, carbamazepine, phenytoin

8 USE IN SPECIFIC POPULATIONS

8.1 Pregnancy

Risk Summary
There are insufficient data on use of fosaprepitant in pregnant women to identify a drug associated risk of major birth defects, miscarriage or other adverse maternal or fetal outcomes. In animal reproduction studies, no adverse developmental effects were observed in rats or rabbits exposed during the period of organogenesis to systemic drug levels (AUC) approximately equivalent to the exposure at the recommended human dose (RHD) of 150 mg (see Data).

The background risk of major birth defects and miscarriage for the indicated populations is unknown. All pregnancies have a background risk of birth defect, loss, or other adverse outcomes. In the U.S. general population, the estimated background risk of major birth defects and miscarriage in clinically recognized pregnancies is 2 to 4% and 15 to 20%, respectively.

Data

Animal Data

In embryofetal development studies in rats and rabbits, aprepitant was administered during the period of organogenesis at oral doses up to 1000 mg/kg twice daily (rats) and up to the maximum tolerated dose of 25 mg/kg/day (rabbits). No embryofetal lethality or malformations were observed at any dose level in either species. The exposures (AUC) in pregnant rats at 1000 mg/kg twice daily and in pregnant rabbits at 25 mg/kg/day were approximately equivalent to the exposure at the RHD of 150 mg. Aprepitant crosses the placenta in rats and rabbits.

8.2 Lactation

Risk Summary

There are no data on the presence of aprepitant in human milk, the effects on the breastfed infant, or the effects on milk production. Aprepitant is present in rat milk. When a drug is present in animal milk, it is likely that the drug will be present in human milk. The developmental and health benefits of breastfeeding should be considered along with the mother’s clinical need for FOCINVEZ and any potential adverse effects on the breastfed infant from FOCINVEZ or from the underlying maternal condition.

8.3 Females and Males of Reproductive Potential

Contraception
Upon administration of FOCINVEZ, the efficacy of hormonal contraceptives may be reduced. Advise females of reproductive potential using hormonal contraceptives to use an effective alternative or back-up non-hormonal contraceptive (such as condoms and spermicides) during treatment with FOCINVEZ and for 1 month following the last dose of fosaprepitant or oral aprepitant [see Drug Interactions (7.1) and Clinical Pharmacology (12.3)] .

8.4 Pediatric Use

The safety and effectiveness of a single dose regimen of FOCINVEZ and a 3-day intravenous fosaprepitant/oral aprepitant/oral aprepitant regimen have been established in pediatric patients 6 months to 17 years for the prevention of acute and delayed nausea and vomiting associated with initial and repeat courses of HEC and MEC.

Use of FOCINVEZ in this age group is supported by evidence from adequate and well-controlled studies of intravenous fosaprepitant in adults, with additional safety, efficacy and pharmacokinetic data in pediatric patients 6 months to 17 years. Efficacy and safety were also supported by data from an adequate and well controlled study of a 3-day oral aprepitant regimen in pediatric patients 6 months to 17 years. See the full prescribing information for aprepitant capsules for complete clinical information regarding studies performed with oral aprepitant. Adverse reactions were similar to those reported in adult patients. [See Dosage and Administration (2.2), Adverse Reactions (6.1), and Clinical Pharmacology (12.3)] .

The safety and effectiveness of FOCINVEZ for the prevention of nausea and vomiting associated with HEC or MEC have not been established in patients less than 6 months of age.

Juvenile Animal Toxicity Data
In juvenile dogs treated with fosaprepitant, changes in reproductive organs were observed. In juvenile rats treated with aprepitant, slight changes in sexual maturation were observed without an effect on reproduction. No effects on neurobehavior, sensory and motor function, or learning and memory were observed in rats.

In a toxicity study in juvenile dogs treated with fosaprepitant from postnatal day 14 (equivalent to a newborn human) to day 42 (approximately equivalent to a 2 year old human), decreased testicular weight and Leydig cell size were seen in the males at 6 mg/kg/day and increased uterine weight, hypertrophy of the uterus and cervix, and edema of vaginal tissues were seen in females from 4 mg/kg/day. A study was also conducted in young rats to evaluate the effects of aprepitant on growth and on neurobehavioral and sexual development. Rats were treated at oral doses up to the maximum feasible dose of 1000 mg/kg twice daily (providing exposure in male and female rats lower than the exposure at the recommended pediatric human dose) from the early postnatal period (Postnatal Day 10 (equivalent to a newborn human) through Postnatal Day 58 (approximately equivalent to a 15 year old human)). Slight changes in the onset of sexual maturation were observed in female and male rats; however, there were no effects on mating, fertility, embryonic-fetal survival, or histomorphology of the reproductive organs. There were no effects in neurobehavioral tests of sensory function, motor function, and learning and memory.

Additional pediatric use information is approved for Merck Sharp & Dohme LLC’s EMEND (fosaprepitant) for injection. However, due to Merck Sharp & Dohme LLC’s marketing exclusivity rights, this drug product is not labeled with that information.

8.5 Geriatric Use

Of the 1649 adult cancer patients treated with intravenous fosaprepitant in HEC and MEC clinical studies, 27% were aged 65 and over, while 5% were aged 75 and over. Other reported clinical experience with fosaprepitant has not identified differences in responses between elderly and younger adult patients. No clinically meaningful differences in the pharmacokinetics of oral aprepitant were observed in healthy subjects 65 years of age and over compared to younger adult subjects [see Clinical Pharmacology (12.3)].

8.6 Patients with Hepatic Impairment

The pharmacokinetics of aprepitant in patients with mild and moderate hepatic impairment were similar to those of healthy subjects with normal hepatic function. No dosage adjustment is necessary for patients with mild to moderate hepatic impairment (Child-Pugh score 5 to 9). There are no clinical or pharmacokinetic data in patients with severe hepatic impairment (Child-Pugh score greater than 9). Therefore, additional monitoring for adverse reactions in these patients may be warranted when FOCINVEZ is administered [see Clinical Pharmacology (12.3)] .

10 OVERDOSAGE

There is no specific information on the treatment of overdosage with fosaprepitant or aprepitant.

In the event of overdose, FOCINVEZ should be discontinued and general supportive treatment and monitoring should be provided.

Aprepitant is not removed by hemodialysis.

11 DESCRIPTION

FOCINVEZ (fosaprepitant injection) is a sterile, ready-to-use, clear and colorless solution formulation containing fosaprepitant dimeglumine, a prodrug of aprepitant, a substance P/neurokinin-1 (NK1) receptor antagonist, an antiemetic agent, chemically described as 1-Deoxy-1-(methylamino)-D-glucitol[3-[[(2R,3S)-2-[(1R)-1-[3,5bis(trifluoromethyl)phenyl]ethoxy]-3-(4-fluorophenyl)-4-morpholinyl]methyl]-2,5-dihydro-5-oxo-1 H-1,2,4triazol-1-yl]phosphonate (2:1) (salt).

Its empirical formula is C23H22F7N4O6P ⋅ 2(C7H17NO5) and its structural formula is:

Fosaprepitant dimeglumine is a white to off-white amorphous powder with a molecular weight of 1004.83. It is freely soluble in water.

Each 50 mL vial of FOCINVEZ for administration as an intravenous infusion contains 150 mg of fosaprepitant (equivalent to 245.3 mg of fosaprepitant dimeglumine) and the following inactive ingredients: Betadex sulfobutyl ether sodium (8 g), edetate disodium (5.4 mg), sodium hydroxide (for pH adjustment) in water for injection.

12 CLINICAL PHARMACOLOGY

12.1 Mechanism of Action

Fosaprepitant is a prodrug of aprepitant and accordingly, its antiemetic effects are attributable to aprepitant.

Aprepitant is a selective high-affinity antagonist of human substance P/neurokinin 1 (NK1) receptors. Aprepitant has little or no affinity for serotonin (5-HT3), dopamine, and corticosteroid receptors, the targets of existing therapies for chemotherapy-induced nausea and vomiting (CINV). Aprepitant has been shown in animal models to inhibit emesis induced by cytotoxic chemotherapeutic agents, such as cisplatin, via central actions. Animal and human Positron Emission Tomography (PET) studies with aprepitant have shown that it crosses the blood brain barrier and occupies brain NK1receptors. Animal and human studies have shown that aprepitant augments the antiemetic activity of the 5-HT3-receptor antagonist ondansetron and the corticosteroid dexamethasone and inhibits both the acute and delayed phases of cisplatin-induced emesis.

12.2 Pharmacodynamics

Cardiac Electrophysiology
In a randomized, double-blind, positive-controlled, thorough QTc study, a single 200-mg dose of fosaprepitant (approximately 1.3 times the recommended dose) had no effect on the QTc interval.

12.3 Pharmacokinetics

Aprepitant after Fosaprepitant Administration
Following administration of a single intravenous 150-mg dose of fosaprepitant, a prodrug of aprepitant administered as a 20-minute infusion to healthy subjects, the mean AUC0-∞of aprepitant was 37.4 (± 14.8) mcg•hr/mL and the mean maximal aprepitant concentration (Cmax) was 4.2 (± 1.2) mcg/mL. Plasma concentrations of fosaprepitant are below the limits of quantification (10 ng/mL) within 30 minutes of the completion of infusion.

Distribution
Aprepitant is greater than 95% bound to plasma proteins. The mean apparent volume of distribution at steady state (Vdss) was approximately 70 L in humans.

Aprepitant crosses the blood brain barrier in humans [see Clinical Pharmacology (12.1)] .

Elimination
Metabolism
Fosaprepitant is converted to aprepitant in in vitro incubations with human liver preparations and in S9 preparations from multiple other human tissues including kidney, lung and ileum. Thus, it appears that the conversion of fosaprepitant to aprepitant can occur in multiple extrahepatic tissues in addition to the liver.

Aprepitant undergoes extensive metabolism. In vitro studies using human liver microsomes indicate that aprepitant is metabolized primarily by CYP3A4 with minor metabolism by CYP1A2 and CYP2C19. Metabolism is largely via oxidation at the morpholine ring and its side chains. No metabolism by CYP2D6, CYP2C9, or CYP2E1 was detected.

In healthy young adults, aprepitant accounts for approximately 24% of the radioactivity in plasma over 72 hours following a single oral 300-mg dose of [^14C]-aprepitant, indicating a substantial presence of metabolites in the plasma. Seven metabolites of aprepitant, which are only weakly active, have been identified in human plasma.

Excretion
Following administration of a single intravenous 100-mg dose of [^14C]-fosaprepitant to healthy subjects, 57% of the radioactivity was recovered in urine and 45% in feces.

Aprepitant is eliminated primarily by metabolism; aprepitant is not renally excreted. The apparent terminal half-life ranged from approximately 9 to 13 hours.

Specific Populations

Geriatric Patients

Following oral administration of a single 125-mg dose of aprepitant on Day 1 and 80 mg once daily on Days 2 through 5, the AUC0-24hr of aprepitant was 21% higher on Day 1 and 36% higher on Day 5 in healthy elderly subjects (65 years and older) relative to younger adult subjects. The Cmax was 10% higher on Day 1 and 24% higher on Day 5 in healthy elderly subjects relative to younger adult subjects. These differences are not considered clinically meaningful [ see Use in Specific Populations (8.5)].

Pediatric Patients

Single-Dose Intravenous Fosaprepitant Regimen: Simulated systemic exposures of aprepitant in patients 2 years to less than 12 years and observed systemic exposures in patients 6 months to less than 2 years and 12 to 17 years are shown in Table 9, including AUC0-24hr, peak plasma concentration (Cmax) on Day 1 and concentrations at the end of Day 1 (C24), Day 2 (C48) and Day 3 (C72).

Table 9 Systemic Exposures of Aprepitant for Single-Dose Intravenous Fosaprepitant Regimen in Pediatric Patients

Population | Single-Dose of Intravenous Fosaprepitant Regimen | Geometric Mean
Population | Single-Dose of Intravenous Fosaprepitant Regimen | AUC0-24hr. (mcg*hr/mL) | Cmax (mcg/mL) | C24 (mcg/mL) | C48 (mcg/mL) | C72 (mcg/mL)
12 Years to 17 Years | 150 mg | 29.4 | 3.4 | 0.7 | NDa | NDa
6 Years to less than 12 Years | 4 mg/kg | 35.2 | 3.6 | 0.7 | 0.2 | 0.05
2 Years to less than 6 Years | 4 mg/kg | 28.2 | 3.1 | 0.4 | 0.1 | 0.02
6 Months to less than 2 Years | 5 mg/kg | 32.7 | 3.3 | 0.4 | NEb | NDa

aND = Not Determined. Pharmacokinetic samples were not collected to support the parameter value of interest.
b NE = Not Estimated. The geometric mean could not be estimated due to values being below the limitation of quantification.

3-Day Intravenous fosaprepitant/Oral aprepitant/Oral aprepitant Regimen:Simulated aprepitant systemic exposures in patients 6 months to less than 12 years and observed systemic exposures in patients 12 to 17 years are shown in Table 10, including AUC0-24hr, peak plasma concentration (Cmax) on Day 1 and concentrations at the end of Day 1 (C24), Day 2 (C48) and Day 3 (C72).

Table 10 Systemic Exposures of Aprepitant for 3-Day Intravenous/Oral/Oral Regimen in Pediatric Patients

Population | 3-Day Dose of fosaprepitant/ aprepitant (IV/Oral/Orala) | Geometric Mean
Population | 3-Day Dose of fosaprepitant/ aprepitant (IV/Oral/Orala) | AUC0-24hr. (mcg*hr/mL) | Cmax (mcg/mL) | C24 (mcg/mL) | C48 (mcg/mL) | C72 (mcg/mL)
12 Years to 17 Years | 115/80/80 mg | 18.0 | 3.0 | 0.4 | 0.2 | NEb
6 Years to less than 12 Years | 3/2/2 mg/kg | 25.7 | 2.7 | 0.5 | 0.3 | 0.3
2 Years to less than 6 Years |  | 20.2 | 2.3 | 0.3 | 0.2 | 0.2
6 Months to less than 2 Years |  | 16.6 | 1.9 | 0.2 | 0.1 | 0.1

a Intravenous fosaprepitant on Day 1, oral aprepitant on Day 2, and oral aprepitant on Day 3
b NE = Not Estimated. The geometric mean could not be estimated due to values being below the limitation of quantification.

Plasma concentrations of fosaprepitant are negligible within 15-30 minutes after the completion of the infusion in pediatric patients.

Male and Female Patients

Following oral administration of a single dose of aprepitant, ranging from 40 mg to 375 mg, the AUC0-24hr and Cmax are 9% and 17% higher in females as compared with males. The half-life of aprepitant is approximately 25% lower in females as compared with males and Tmax occurs at approximately the same time. These differences are not considered clinically meaningful. A population pharmacokinetic analysis of aprepitant in pediatric patients (6 months to 17 years) suggests that sex has no clinically meaningful effect on the pharmacokinetics of aprepitant.

Racial and Ethnic Groups

Following oral administration of a single dose of aprepitant, ranging from 40 mg to 375 mg, the AUC0-24hr and Cmax are approximately 27% and 19% higher in Hispanics as compared with Caucasians. The AUC0-24hr and Cmax were 74% and 47% higher in Asians as compared to Caucasians. There was no difference in AUC0-24hr or Cmax between Caucasians and Blacks. These differences are not considered clinically meaningful. A population pharmacokinetic analysis of aprepitant in pediatric patients (6 months to 17 years) suggests that race has no clinically meaningful effect on the pharmacokinetics of aprepitant.

Patients with Renal Impairment

A single 240-mg oral dose of aprepitant was administered to patients with severe renal impairment (creatinine clearance less than 30 mL/min/1.73 m^2 as measured by 24-hour urinary creatinine clearance) and to patients with end stage renal disease (ESRD) requiring hemodialysis.

In patients with severe renal impairment, the AUC0-∞ of total aprepitant (unbound and protein bound) decreased by 21% and Cmax decreased by 32%, relative to healthy subjects (creatinine clearance greater than 80 mL/min estimated by Cockcroft-Gault method). In patients with ESRD undergoing hemodialysis, the AUC0-∞ of total aprepitant decreased by 42% and Cmax decreased by 32%. Due to modest decreases in protein binding of aprepitant in patients with renal disease, the AUC of pharmacologically active unbound drug was not significantly affected in patients with renal impairment compared with healthy subjects. Hemodialysis conducted 4 or 48 hours after dosing had no significant effect on the pharmacokinetics of aprepitant; less than 0.2% of the dose was recovered in the dialysate.

Patients with Hepatic Impairment

Fosaprepitant is metabolized in various extrahepatic tissues; therefore, hepatic impairment is not expected to alter the conversion of fosaprepitant to aprepitant.

Following administration of a single 125-mg oral dose of aprepitant on Day 1 and 80 mg once daily on Days 2 and 3 to patients with mild hepatic impairment (Child-Pugh score 5 to 6), the AUC0-24hr of aprepitant was 11% lower on Day 1 and 36% lower on Day 3, as compared with healthy subjects given the same regimen. In patients with moderate hepatic impairment (Child-Pugh score 7 to 9), the AUC0-24hr of aprepitant was 10% higher on Day 1 and 18% higher on Day 3, as compared with healthy subjects given the same regimen. These differences in AUC0-24hr are not considered clinically meaningful.

There are no clinical or pharmacokinetic data in patients with severe hepatic impairment (Child-Pugh score greater than 9) [see Use in Specific Populations (8.6)].

Body Mass Index (BMI)

For every 5 kg/m^2 increase in BMI, AUC0-24hr and Cmax of aprepitant decrease by 9% and 10%. BMI of subjects in the analysis ranged from 18 kg/m^2 to 36 kg/m^2. This change is not considered clinically meaningful.

Drug Interaction Studies

Fosaprepitant, given as a single 150-mg dose, is a weak inhibitor of CYP3A4, with no evidence of inhibition or induction of CYP3A4 observed on Day 4. The weak inhibition of CYP3A4 continues for 2 days after single dose administration of fosaprepitant. Aprepitant is a substrate, an inhibitor, and an inducer of CYP3A4. Aprepitant is also an inducer of CYP2C9.

Fosaprepitant or aprepitant is unlikely to interact with drugs that are substrates for the P-glycoprotein transporter.

Effects of Fosaprepitant/Aprepitant on the Pharmacokinetics of Other Drugs

CYP3A4 Substrates

Midazolam: Fosaprepitant 150 mg administered as a single intravenous dose on Day 1 increased the AUC0-∞ of midazolam by approximately 1.8-fold on Day 1 and had no effect on Day 4 when midazolam was coadministered as a single oral dose of 2 mg on Days 1 and 4 [see Drug Interactions (7.1)].

Corticosteroids:

Dexamethasone: Fosaprepitant administered as a single 150 mg intravenous dose on Day 1 increased the AUC0-24hr of dexamethasone, administered as a single 8-mg oral dose on Days 1, 2, and 3, by approximately 2-fold on Days 1 and 2 [see Dosage and Administration (2.1) and Drug Interactions (7.1)].

Methylprednisolone: When oral aprepitant as a 3-day regimen (125-mg/80-mg/80-mg) was administered with intravenous methylprednisolone 125 mg on Day 1 and oral methylprednisolone 40 mg on Days 2 and 3, the AUC of methylprednisolone was increased by 1.34-fold on Day 1 and by 2.5-fold on Day 3 [see Drug Interactions (7.1)].

Chemotherapeutic agents:

Docetaxel: In a pharmacokinetic study, oral aprepitant administered as a 3-day regimen (125mg/80-mg/80-mg) did not influence the pharmacokinetics of docetaxel.

Vinorelbine: In a pharmacokinetic study, oral aprepitant administered as a 3-day regimen (125mg/80-mg/80-mg) did not influence the pharmacokinetics of vinorelbine to a clinically significant degree.

Oral contraceptives: When oral aprepitant was administered as a 3-day regimen (125-mg/80mg/80-mg) with ondansetron and dexamethasone, and coadministered with an oral contraceptive containing ethinyl estradiol and norethindrone, the trough concentrations of both ethinyl estradiol and norethindrone were reduced by as much as 64% for 3 weeks post-treatment [see Drug Interactions (7.1)] .

CYP2C9 substrates (Warfarin, Tolbutamide):
Warfarin: A single 125-mg dose of oral aprepitant was administered on Day 1 and 80 mg/day on Days 2 and 3 to subjects who were stabilized on chronic warfarin therapy. Although there was no effect of oral aprepitant on the plasma AUC of R(+) or S(-) warfarin determined on Day 3, there was a 34% decrease in S(-) warfarin trough concentration accompanied by a 14% decrease in the prothrombin time (reported as International Normalized Ratio or INR) 5 days after completion of dosing with oral aprepitant [see Drug Interactions (7.1)] .

Tolbutamide: Oral aprepitant, when given as 125 mg on Day 1 and 80 mg/day on Days 2 and 3, decreased the AUC of tolbutamide by 23% on Day 4, 28% on Day 8, and 15% on Day 15, when a single dose of tolbutamide 500 mg was administered prior to the administration of the 3-day regimen of oral aprepitant and on Days 4, 8, and 15. This effect was not considered clinically important.

Other Drugs

P-glycoprotein substrates: Aprepitant is unlikely to interact with drugs that are substrates for the P-glycoprotein transporter, as demonstrated by the lack of interaction of oral aprepitant with digoxin in a clinical drug interaction study.

5-HT3 antagonists: In clinical drug interaction studies, aprepitant did not have clinically important effects on the pharmacokinetics of ondansetron, granisetron, or hydrodolasetron (the active metabolite of dolasetron).

Effect of Other Drugs on the Pharmacokinetics of Fosaprepitant/Aprepitant

Rifampin: When a single 375-mg dose of oral aprepitant was administered on Day 9 of a 14-day regimen of 600 mg/day of rifampin, a strong CYP3A4 inducer, the AUC of aprepitant decreased approximately 11-fold and the mean terminal half-life decreased approximately 3-fold [see Drug Interactions (7.2)] .

Ketoconazole: When a single 125-mg dose of oral aprepitant was administered on Day 5 of a 10-day regimen of 400 mg/day of ketoconazole, a strong CYP3A4 inhibitor, the AUC of aprepitant increased approximately 5-fold and the mean terminal half-life of aprepitant increased approximately 3-fold [see Drug Interactions (7.2)] .

Diltiazem: In a study in 10 patients with mild to moderate hypertension, administration of 100 mg of fosaprepitant as an intravenous infusion with 120 mg of diltiazem, a moderate CYP3A4 inhibitor administered three times daily, resulted in a 1.5-fold increase in the aprepitant AUC and a 1.4-fold increase in the diltiazem AUC.

When fosaprepitant was administered with diltiazem, the mean maximum decrease in diastolic blood pressure was significantly greater than that observed with diltiazem alone [24.3 ± 10.2 mm Hg with fosaprepitant versus 15.6 ± 4.1 mm Hg without fosaprepitant]. The mean maximum decrease in systolic blood pressure was also greater after co-administration of diltiazem with fosaprepitant than administration of diltiazem alone [29.5 ± 7.9 mm Hg with fosaprepitant versus 23.8 ± 4.8 mm Hg without fosaprepitant]. Co-administration of fosaprepitant and diltiazem; however, did not result in any additional clinically significant changes in heart rate or PR interval, beyond those changes observed with diltiazem alone [see Drug Interactions (7.2)].

Paroxetine: Coadministration of once daily doses of oral aprepitant 170 mg, with paroxetine 20 mg once daily, resulted in a decrease in AUC by approximately 25% and Cmax by approximately 20% of both aprepitant and paroxetine. This effect was not considered clinically important.

Additional pediatric use information is approved for Merck Sharp & Dohme LLC’s EMEND (fosaprepitant) for injection. However, due to Merck Sharp & Dohme LLC’s marketing exclusivity rights, this drug product is not labeled with that information.

13 NONCLINICAL TOXICOLOGY

13.1 Carcinogenesis, Mutagenesis, Impairment of Fertility

Carcinogenesis

Carcinogenicity studies were conducted in Sprague-Dawley rats and in CD-1 mice for 2 years. In the rat carcinogenicity studies, animals were treated with oral doses ranging from 0.05 to 1000 mg/kg twice daily. The highest dose produced systemic exposures to aprepitant approximately equivalent to (female rats) or less than (male rats) the adult human exposure at the RHD of 150 mg. Treatment with aprepitant at doses of 5 to 1000 mg/kg twice daily caused an increase in the incidences of thyroid follicular cell adenomas and carcinomas in male rats. In female rats, it produced hepatocellular adenomas at 5 to 1000 mg/kg twice daily and hepatocellular carcinomas and thyroid follicular cell adenomas at 125 to 1000 mg/kg twice daily. In the mouse carcinogenicity studies, the animals were treated with oral doses ranging from 2.5 to 2000 mg/kg/day. The highest dose produced a systemic exposure approximately 2 times the adult human exposure at the RHD of 150 mg. Treatment with aprepitant produced skin fibrosarcomas at 125 and 500 mg/kg/day doses in male mice. Carcinogenicity studies were not conducted with fosaprepitant.

Mutagenesis

Aprepitant and fosaprepitant were not genotoxic in the Ames test, the human lymphoblastoid cell (TK6) mutagenesis test, the rat hepatocyte DNA strand break test, the Chinese hamster ovary (CHO) cell chromosome aberration test and the mouse micronucleus test.

Impairment of Fertility

Fosaprepitant, when administered intravenously, is rapidly converted to aprepitant. In the fertility studies conducted with fosaprepitant and aprepitant, the highest systemic exposures to aprepitant were obtained following oral administration of aprepitant. Oral aprepitant did not affect the fertility or general reproductive performance of male or female rats at doses up to the maximum feasible dose of 1000 mg/kg twice daily (providing exposure in male rats lower than the exposure at the recommended adult human dose of 150 mg and exposure in female rats approximately equivalent to the adult human exposure).

14 CLINICAL STUDIES

The safety and efficacy of FOCINVEZ have been established based on adequate and well-controlled adult studies of another intravenous formulation of fosaprepitant for the prevention and of chemotherapy induced nausea and vomiting. Below is a description of the results of these adequate and well-controlled studies of fosaprepitant.

14.1 Prevention of Nausea and Vomiting Associated with HEC in Adults

In a randomized, parallel, double-blind, active-controlled study, fosaprepitant 150 mg as a single intravenous infusion (N=1147) was compared to a 3-day oral aprepitant regimen (N=1175) in patients receiving a HEC regimen that included cisplatin (70 mg/m^2). All patients in both groups received dexamethasone and ondansetron (see Table 11). Patient demographics were similar between the two treatment groups. Of the total 2322 patients, 63% were men, 56% White, 26% Asian, 3% American Indian/Alaska Native, 2% Black, 13% Multi-Racial, and 33% Hispanic/Latino ethnicity. Patient ages ranged from 19 to 86 years of age, with a mean age of 56 years. Other concomitant chemotherapy agents commonly administered were fluorouracil (17%), gemcitabine (16%), paclitaxel (15%), and etoposide (12%).

Table 11 Treatment Regimens in Adult HEC Triala

 | Day 1 | Day 2 | Day 3 | Day 4
Fosaprepitant Regimen
intravenous fosaprepitant | 150 mg intravenously over 20 to 30 minutes approximately 30 minutes prior to chemotherapy | none | none | none
Oral dexamethasoneb | 12 mg | 8 mg | 8 mg twice daily | 8 mg twice daily
Ondansetron | Ondansetronc | none | none | none
Oral aprepitant Regimen
Aprepitant capsules | 125 mg | 80 mg | 80 mg | none
Oral dexamethasoned | 12 mg | 8 mg | 8 mg | 8 mg
Ondansetron | Ondansetronc | none | none | none

a Intravenous fosaprepitant placebo, aprepitant capsules placebo and dexamethasone placebo (in the evenings on Days 3 and 4) were used to maintain blinding.
b Dexamethasone was administered 30 minutes prior to chemotherapy treatment on Day 1 and in the morning on Days 2 through 4. Dexamethasone was also administered in the evenings on Days 3 and 4. The 12 mg dose of dexamethasone on Day 1 and the 8 mg once daily dose on Day 2 reflects a dosage adjustment to account for a drug interaction with the intravenous fosaprepitant regimen [see Clinical Pharmacology (12.3)] .
c Ondansetron 32 mg intravenous was used in the clinical trials of intravenous fosaprepitant. Although this dose was used in clinical trials, this is no longer the currently recommended dose. Refer to the ondansetron prescribing information for the current recommended dose.
d Dexamethasone was administered 30 minutes prior to chemotherapy treatment on Day 1 and in the morning on Days 2 through 4. The 12 mg dose of dexamethasone on Day 1 and the 8 mg once daily dose on Days 2 through 4 reflects a dosage adjustment to account for a drug interaction with the oral aprepitant regimen [see Clinical Pharmacology (12.3)] .

The efficacy of intravenous fosaprepitant was evaluated based on the primary and secondary endpoints listed in Table 12 and was shown to be non-inferior to that of the 3-day oral aprepitant regimen with regard to complete response in each of the evaluated phases. The pre-specified non-inferiority margin for complete response in the overall phase was 7%. The pre-specified non-inferiority margin for complete response in the delayed phase was 7.3%. The pre-specified non-inferiority margin for no vomiting in the overall phase was 8.2%.

Table 12

Percent of Adult Patients Receiving HEC Responding by Treatment Group and Phase - Cycle 1

ENDPOINTS | Intravenous fosaprepitant Regimen (N = 1106)a % | Oral aprepitant Regimen (N = 1134)a % | Differenceb (95% CI)
PRIMARY ENDPOINT
Complete Responsec
Overalld | 71.9 | 72.3 | -0.4 (-4.1, 3.3)
SECONDARY ENDPOINTS
Complete Responsec
Delayed phasee | 74.3 | 74.2 | 0.1 (-3.5, 3.7)
No Vomiting
Overalld | 72.9 | 74.6 | -1.7 (-5.3, 2.0)

a N: Number of patients included in the primary analysis of complete response.
bDifference and Confidence interval (CI) were calculated using the method proposed by Miettinen and Nurminen and adjusted for Gender.
c Complete Response = no vomiting and no use of rescue therapy.
d Overall = 0 to 120 hours post-initiation of cisplatin chemotherapy.
e Delayed phase = 25 to 120 hours post-initiation of cisplatin chemotherapy.

14.2 Prevention of Nausea and Vomiting Associated with MEC in Adults

In a randomized, parallel, double-blind, active comparator-controlled study, intravenous fosaprepitant 150 mg as a single intravenous infusion (N=502) in combination with ondansetron and dexamethasone (intravenous fosaprepitant regimen) was compared with ondansetron and dexamethasone alone (standard therapy) (N=498) (see Table 13) in patients receiving a MEC regimen. Patient demographics were similar between the two treatment groups. Of the total 1,000 patients included in the efficacy analysis, 41% were men, 84% White, 4% Asian, 1% American Indian/Alaska Native, 2% Black, 10% Multi-Racial, and 19% Hispanic/Latino ethnicity. Patient ages ranged from 23 to 88 years of age, with a mean age of 60 years. The most commonly administered MEC chemotherapeutic agents were carboplatin (51%), oxaliplatin (24%), and cyclophosphamide (12%).

Table 13 Treatment Regimens in Adult MEC Triala

 | Day 1 | Day 2 | Day 3
Intravenous fosaprepitant Regimen
Intravenous fosaprepitant | 150 mg intravenously over 20 to 30 minutes approximately 30 minutes prior to chemotherapy | none | none
Oral Dexamethasoneb | 12 mg | none | none
Oral Ondansetronc | 8 mg for 2 doses | none | none
Standard Therapy
Oral Dexamethasone | 20 mg | none | none
Oral Ondansetronc | 8 mg for 2 doses | 8 mg twice daily | 8 mg twice daily

aIntravenous fosaprepitant placebo and dexamethasone placebo (on Day 1) were used to maintain blinding.
bDexamethasone was administered 30 minutes prior to chemotherapy treatment on Day 1. The 12 mg dose reflects a dosage adjustment to account for a drug interaction with the Intravenous fosaprepitant regimen [see Clinical Pharmacology (12.3)] .
cThe first ondansetron dose was administered 30 to 60 minutes prior to chemotherapy treatment on Day 1 and the second dose was administered 8 hours after first ondansetron dose.

The primary endpoint was complete response (defined as no vomiting and no rescue therapy) in the delayed phase (25 to 120 hours) of chemotherapy-induced nausea and vomiting. The results by treatment group are shown in Table 14.

Table 14 Percent of Adult Patients Receiving MEC Responding by Treatment Group

ENDPOINTS | Intravenous fosaprepitant Regimen (N = 502)a % | Standard Therapy Regimen (N = 498)a % | P-Value | Treatment Difference (95% CI)
PRIMARY ENDPOINT
Complete Responseb
Delayed phasec | 78.9 | 68.5 | <0.001 | 10.4 (5.1, 15.9)

aN: Number of patients included in the intention to treat population.
bComplete Response = no vomiting and no use of rescue therapy.
cDelayed phase = 25 to 120 hours post-initiation of chemotherapy.

16 HOW SUPPLIED/STORAGE AND HANDLING

FOCINVEZ (fosaprepitant injection) contains 150 mg/50 mL of fosaprepitant as a clear and colorless ready-to-use injection solution in a single-dose vial. Supplied as follows:

NDC 82449-231-01 1 vial per carton.

Storage

- Refrigerate FOCINVEZ at 2°C to 8°C (36°F to 46°F).

- FOCINVEZ vials, when kept in original carton, can remain at room temperature 20°C to 25°C (68°F to 77°F) for up to 90 days.

17 PATIENT COUNSELING INFORMATION

Advise the patient to read the FDA-approved patient labeling (Patient Information).

Hypersensitivity

Advise patients that hypersensitivity reactions, including anaphylaxis and anaphylactic shock, have been reported in patients taking fosaprepitant. Advise patients to seek immediate medical attention if they experience signs or symptoms of a hypersensitivity reaction, such as hives, rash and itching, skin peeling or sores, flushing, difficulty in breathing or swallowing, or dizziness, rapid or weak heartbeat or feeling faint [see Warnings and Precautions (5.2)] .

Infusion Site Reactions

Advise patients to seek medical attention if they experience new or worsening signs or symptoms of an infusion site reaction, such as erythema, edema, pain, necrosis, vasculitis, or thrombophlebitis at or near the infusion site [see Warnings and Precautions (5.3)] .

Drug Interactions

Advise patients to discuss all medications they are taking, including other prescription, nonprescription medication or herbal products [see Contraindications (4) and Warnings and Precautions (5.1)] .

Warfarin: Instruct patients on chronic warfarin therapy to follow instructions from their healthcare provider regarding blood draws to monitor their INR during the 2-week period, particularly at 7 to 10 days, following initiation of FOCINVEZ with each chemotherapy cycle [see Warnings and Precautions (5.4)] .

Hormonal Contraceptives: Advise patients that administration of FOCINVEZ may reduce the efficacy of hormonal contraceptives. Instruct patients to use effective alternative or back-up methods of contraception (such as condoms and spermicides) during treatment with FOCINVEZ and for 1 month following administration of the last dose of fosaprepitant or oral aprepitant [see Warnings and Precautions (5.5) and Use in Specific Populations(8.3)] .

Manufactured for:

Steriscience Pte. Limited

Manufactured by:

OneSource Specialty Pharma Limited
Sterile Product Division, Opp IIM, Bilekahalli,
Bannerghatta Road, Bengaluru, India 560076

Patient Information
FOCINVEZ (FOR sin vez)
(fosaprepitant injection), for intravenous use

Read this Patient Information before you start receiving FOCINVEZ and each time you are scheduled to receive FOCINVEZ. There may be new information. This information does not take the place of talking with your healthcare provider about your medical condition or treatment.

What is FOCINVEZ?
FOCINVEZ is a prescription medicine used with other medicines that treat nausea and vomiting in patients 6 months of age and older to prevent nausea and vomiting caused by certain anti-cancer (chemotherapy) medicines.

- FOCINVEZ is not used to treat nausea and vomiting that you already have.
- It is not known if FOCINVEZ is safe and effective in children less than 6 months of age.

Who should not receive FOCINVEZ?
Do not receive FOCINVEZ if you:

- are allergic to fosaprepitant, aprepitant, or any of the ingredients in FOCINVEZ. See the end of this patient information leaflet for a complete list of the ingredients in FOCINVEZ.
- are taking pimozide (ORAP)

What should I tell my healthcare provider before receiving FOCINVEZ?
Before receiving FOCINVEZ, tell your healthcare provider if you:

- have liver problems.
- are pregnant or plan to become pregnant. It is not known if FOCINVEZ can harm your unborn baby.
  - Women who use birth control medicines containing hormones to prevent pregnancy (birth control pills, skin patches, implants, and certain IUDs) should also use a backup method of birth control that does not contain hormones, such as condoms and spermicides, during treatment with FOCINVEZ and for 1 month after receiving the last dose of fosaprepitant or aprepitant.
- are breastfeeding or plan to breastfeed. It is not known if FOCINVEZ passes into your breast
  milk. Talk to your healthcare provider about the best way to feed your baby if you receive
  FOCINVEZ.

Tell your healthcare provider about all the medicines you take, including prescription and over-the-counter medicines, vitamins, and herbal supplements.
FOCINVEZ may affect the way other medicines work, and other medicines may affect the way FOCINVEZ works, causing serious side effects.

Know the medicines you take. Keep a list of them to show your healthcare provider or pharmacist when you get a new medicine.

How will I receive FOCINVEZ?
Adults 18 years of age and older:
FOCINVEZ will be given on Day 1 of chemotherapy treatment. It will be given to you by intravenous (IV) infusion in your vein about 50 to 60 minutes before you start your chemotherapy treatment.

Children 6 months to 17 years of age:
FOCINVEZ will be given to your child by intravenous (IV) infusion into a large vein through a type of IV line called a central venous catheter, about 1 hour to 1 ½ hours before the start of their chemotherapy treatment.
Depending on the chemotherapy treatment, there are 2 ways that FOCINVEZ may be given:

1. FOCINVEZ is given on Day 1 only (single day of chemotherapy).
2. FOCINVEZ is given on Day 1 (single or multiple days of chemotherapy).

- Your child may also receive capsules of aprepitant or an oral suspension of aprepitant on Days 2 and 3. If your child will receive either of these, see the Patient Information for aprepitant capsules or aprepitant for oral suspension for further information.

If you take the blood thinner medicine warfarin sodium (COUMADIN, JANTOVEN), your healthcare provider may do blood tests after you receive FOCINVEZ to check your blood clotting.

What are the possible side effects of FOCINVEZ?
FOCINVEZ may cause serious side effects, including:

- Serious allergic reactions.Allergic reactions can happen with FOCINVEZ and may be serious. Tell your doctor or nurse right away if you have hives, rash, itching, flushing or redness of your face or skin, trouble breathing or swallowing, dizziness, a rapid or weak heartbeat, or you feel faint during or soon after you receive FOCINVEZ, as you may need emergency medical care.
- Severe skin reactions, which may include rash, skin peeling, or sores, may occur.

- Infusion site reactions (ISR) at or near the infusion site have happened with FOCINVEZ.

Most severe ISR have happened with a certain type of chemotherapy medicine that can burn or blister your skin (vesicant) with side effects, including pain, swelling and redness. Death of skin tissue (necrosis) has happened in some people getting this type of chemotherapy medicine. Most ISR can happen with the first, second, or third dose and some can last up to 2 weeks or longer. Tell your healthcare provider right away if you get any infusion site side effects.

In adults, the most common side effects of FOCINVEZ include:

- tiredness
- diarrhea
- low white blood cell and red blood cell counts
- weakness
- feeling weak or numb in your arms and legs

- painful, difficult, or changes in your digestion (dyspepsia)
- urinary tract infection
- pain in your arms and legs

In children 6 months to 17 years of age, the most common side effects of FOCINVEZ include:

- low red blood cell count
- low white blood cell count

- low blood platelet count
- low white blood cell count with a fever

Tell your healthcare provider if you have any side effect that bothers you or that does not go away. These are not all of the possible side effects of FOCINVEZ. For more information ask your healthcare provider or pharmacist.

Call your doctor for medical advice about side effects. You may report side effects to FDA at 1-800-FDA-1088.

General information about the safe and effective use of FOCINVEZ.

If you would like more information about FOCINVEZ, talk with your healthcare provider. You can ask your healthcare provider or pharmacist for information about FOCINVEZ that is written for health professionals. For more information about FOCINVEZ call 1-888-278-1784.

What are the ingredients in FOCINVEZ?
Active ingredient: fosaprepitant
Inactive ingredients: betadex sulfobutyl ether sodium, edetate disodium, sodium hydroxide (for pH adjustment) and water for injection

Additional pediatric use information is approved for Merck Sharp & Dohme LLC’s EMEND (fosaprepitant) for injection. However, due to Merck Sharp & Dohme LLC’s marketing exclusivity rights, this drug product is not labeled with that information

Manufactured for:

Steriscience Pte. Limited

Manufactured by:

OneSource Specialty Pharma Limited
Sterile Product Division, Opp IIM, Bilekahalli,
Bannerghatta Road, Bengaluru, India 560076

This Patient Information has been approved by the U.S. Food and Drug Administration

Issue Date: 10/2025